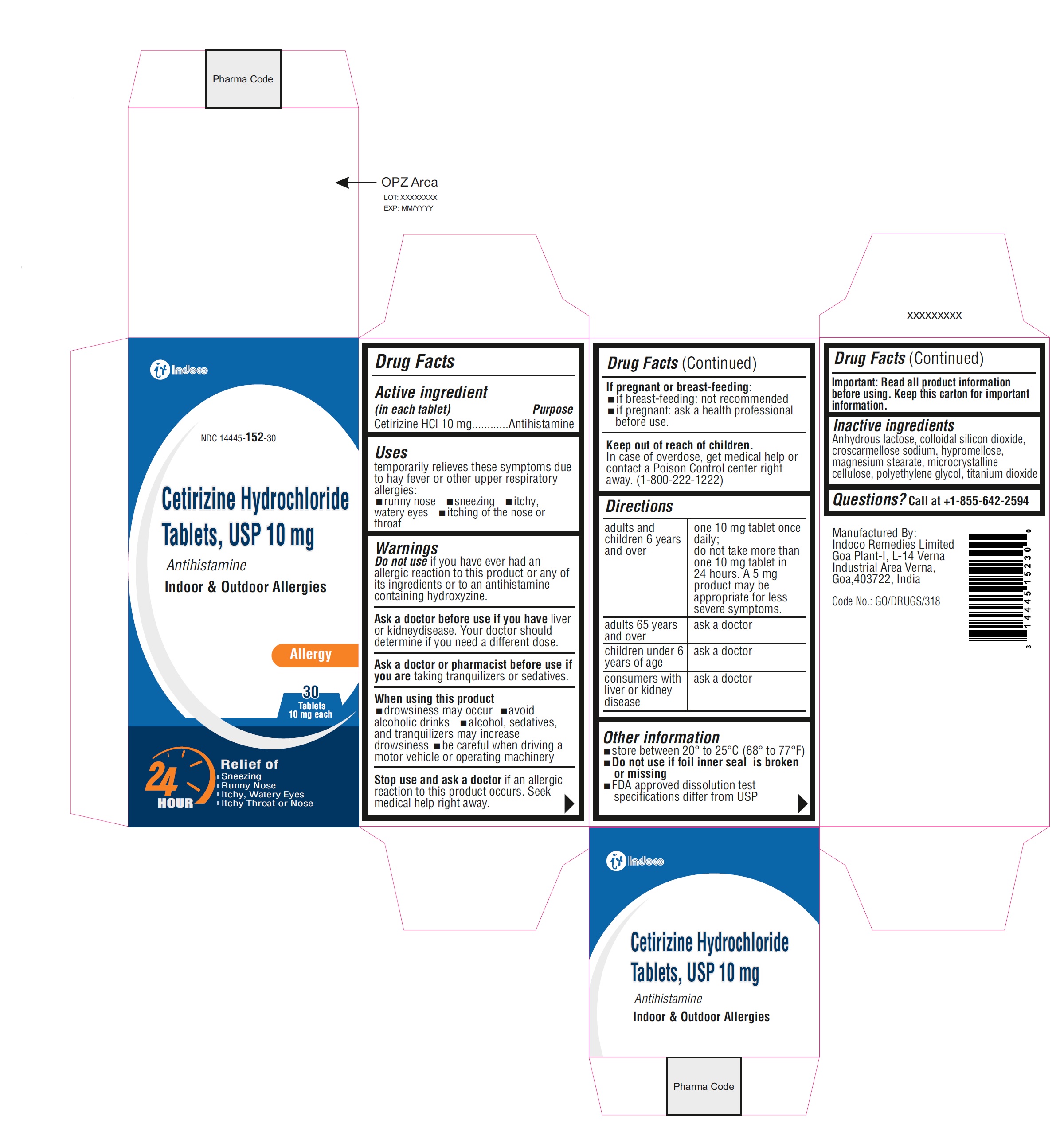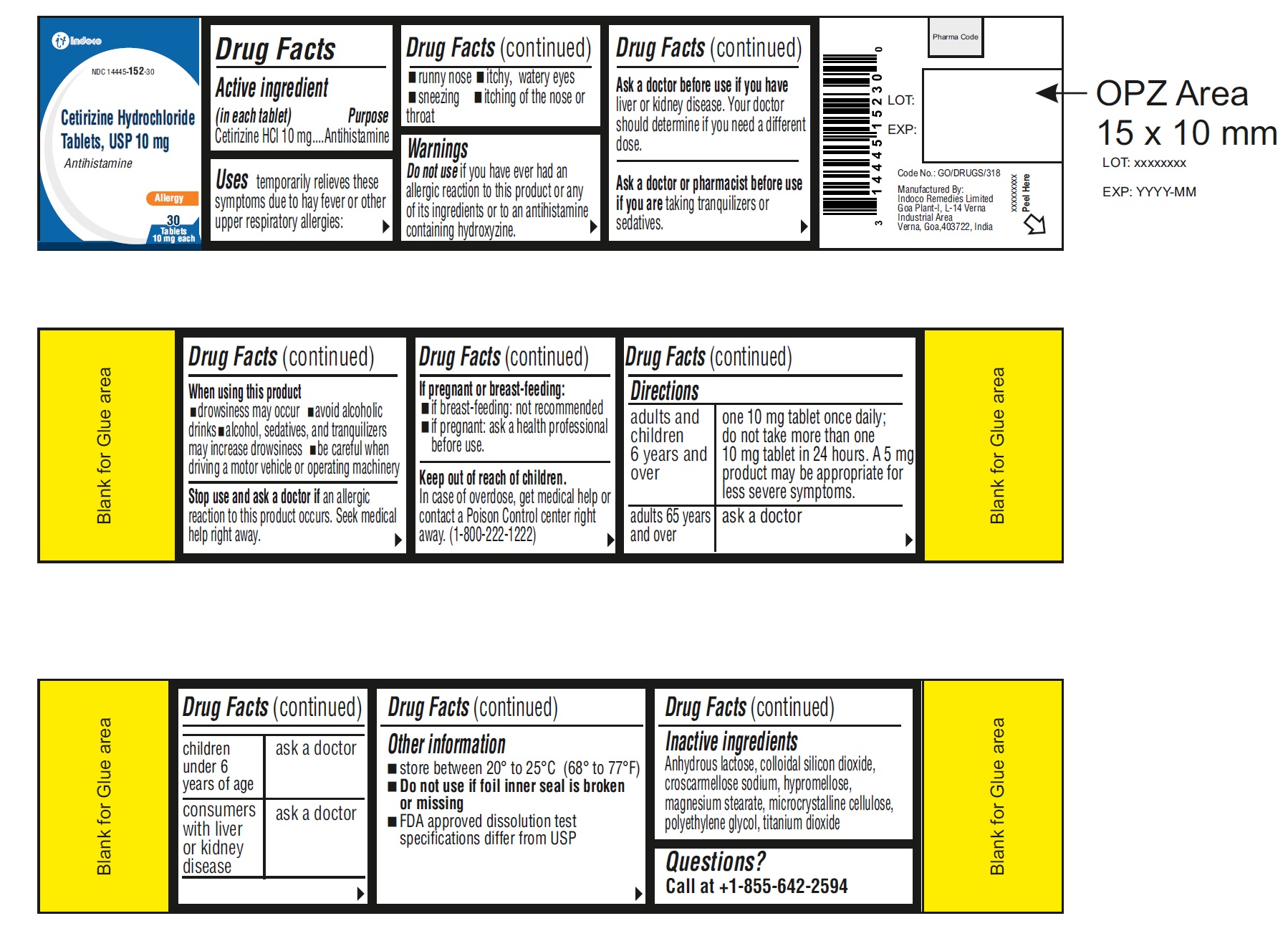 DRUG LABEL: CETIRIZINE HYDROCHLORIDE
NDC: 14445-152 | Form: TABLET, FILM COATED
Manufacturer: Indoco Remedies Limited 
Category: otc | Type: Human OTC Drug Label
Date: 20241007

ACTIVE INGREDIENTS: CETIRIZINE HYDROCHLORIDE 10 mg/1 1
INACTIVE INGREDIENTS: ANHYDROUS LACTOSE; CELLULOSE, MICROCRYSTALLINE; CROSCARMELLOSE SODIUM; SILICON DIOXIDE; MAGNESIUM STEARATE; HYPROMELLOSE 2910 (6 MPA.S); TITANIUM DIOXIDE; POLYETHYLENE GLYCOL 400

Cetirizine Tablets 10 mg
Drugs Facts

ACTIVE INGREDIENT(S)

Cetirizine HCl 10 mg

PURPOSE

Antihistamine

USE(S)

temporarily relieves these symptoms due to hay fever or other upper respiratory allergies:
• runny nose
• sneezing
• itchy, watery eyes
• itching of the nose or throat

WARNINGS

Do not use if you have ever had an allergic reaction to this product or any of its ingredients or to an antihistamine containing hydroxyzine.

Ask a doctor before use if you have liver or kidney disease. Your doctor should determine if you need a different dose.

Ask a doctor or pharmacist before use if you are taking tranquilizers or sedatives.

When using this product

- drowsiness may occur
- avoid alcoholic drinks
- alcohol, sedatives, and tranquilizers may increase drowsiness
- be careful when driving a motor vehicle or operating machinery

Stop use and ask a doctor if an allergic reaction to this product occurs. Seek medical help right away.

If pregnant or breast-feeding

- if breast-feeding: not recommended
- if pregnant: ask a health professional before use.

Keep out of reach of children. In case of overdose, get medical help or contact a Poison Control Center right away. (1-800-222-1222)

DIRECTIONS

adults and children 6 years and over | one 10 mg tablet once daily; do not take more than one 10 mg tablet in 24 hours. A 5 mg product may be appropriate for less severe symptoms.
adults 65 years and over | ask a doctor
children under 6 years of age | ask a doctor
consumers with liver or kidney disease | ask a doctor

Other information

- store between 20° to 25°C (68° to 77°F)
- do not use if foil inner seal is broken or missing
- FDA approved dissolution test specifications differ from USP

Inactive ingredients

anhydrous lactose, colloidal silicon dioxide, croscarmellose sodium, hypromellose, magnesium stearate, microcrystalline cellulose, polyethylene glycol, titanium dioxide

Questions?

Call at +1-855-642-2594

PRINCIPAL DISPLAY PANEL

Original Prescription Strength
NDC 14445-152-30
Cetirizine Hydrochloride Tablets
ALLERGY
Cetirizine HCl tablets
10 mg /antihistamine
Indoor & Outdoor Allergies
24 hour Relief of
• runny nose
• sneezing
• itchy, watery eyes
• itchy throat or nose
30 Tablets
10 mg each

Container Label:

Carton Label: